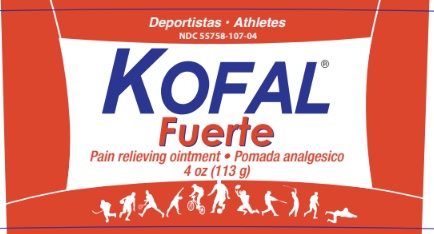 DRUG LABEL: Kofal Fuerte
NDC: 55758-107 | Form: OINTMENT
Manufacturer: Pharmadel LLC
Category: otc | Type: HUMAN OTC DRUG LABEL
Date: 20251204

ACTIVE INGREDIENTS: METHYL SALICYLATE 15 g/100 g
INACTIVE INGREDIENTS: GLYCERYL MONOSTEARATE; PROPYLPARABEN; WATER; TROLAMINE; PARAFFIN; EUCALYPTUS OIL; MENTHOL, UNSPECIFIED FORM; STEARIC ACID; CAMPHOR, (-)-; CETYL ALCOHOL; METHYLPARABEN; POLYSORBATE 20

Kofal Fuerte Rojo 4 Oz (WP)(DA)

Drug Facts

Active ingredient and Purpose

Active ingredient | Purpose
Mythyl Salicylate 15% | Topical analgesic

Use

For the temporary relief of minor aches and pains of muscles and joints associated with

- backaches
- arthritis
- strains
- bruises
- sprains

Warnings

For external use only. Avoid contact with the eyes

Do not

- apply to wounds or damaged skin
- bandage tightly

Stop use and ask a doctor if

condition worsens, or if symptoms persist for more than 7 days or clear up and occur again within a few days.

If pregnant or breast feeding,

ask a health professional before use.

Keep out of reach of children

If swallowed, get medical help, or contact a Poison Control Center immediately.

Directions

- adults and children 2 years of age and older: apply to affected area not more than 3 to 4 times daily
- children under 2 years of age: consult a doctor

Other information

- store in a cool dry place between (59-86°F)15-30°C
- don’t use if seal over jar is broken, torn, or missing

Principal Display Panel

KOFAL ® Fuerte

Deportistas - Athletes

Pain relieving ointment

Pomada analgesico

4 oz (113 g)